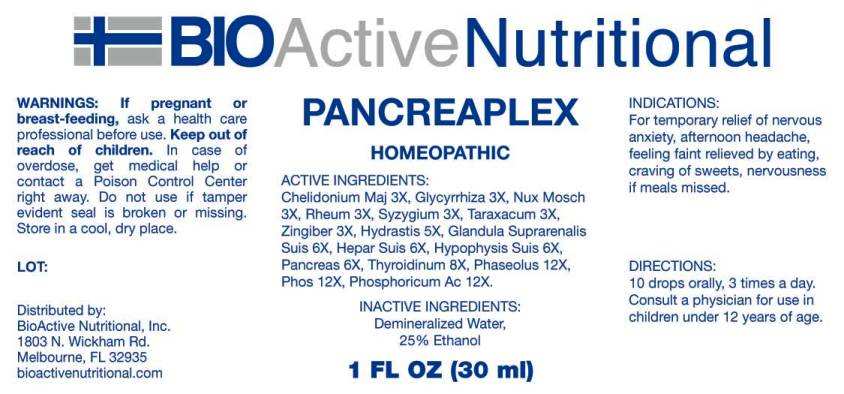 DRUG LABEL: Pancreaplex
NDC: 43857-0590 | Form: LIQUID
Manufacturer: BioActive Nutritional, Inc.
Category: homeopathic | Type: HUMAN OTC DRUG LABEL
Date: 20230605

ACTIVE INGREDIENTS: CHELIDONIUM MAJUS WHOLE 3 [hp_X]/1 mL; GLYCYRRHIZA GLABRA 3 [hp_X]/1 mL; NUTMEG 3 [hp_X]/1 mL; RHEUM PALMATUM ROOT 3 [hp_X]/1 mL; SYZYGIUM CUMINI SEED 3 [hp_X]/1 mL; TARAXACUM OFFICINALE 3 [hp_X]/1 mL; GINGER 3 [hp_X]/1 mL; GOLDENSEAL 5 [hp_X]/1 mL; SUS SCROFA ADRENAL GLAND 6 [hp_X]/1 mL; PORK LIVER 6 [hp_X]/1 mL; SUS SCROFA PITUITARY GLAND 6 [hp_X]/1 mL; SUS SCROFA PANCREAS 6 [hp_X]/1 mL; THYROID 8 [hp_X]/1 mL; KIDNEY BEAN 12 [hp_X]/1 mL; PHOSPHORIC ACID 12 [hp_X]/1 mL; PHOSPHORUS 12 [hp_X]/1 mL
INACTIVE INGREDIENTS: WATER; ALCOHOL

DRUG FACTS:

ACTIVE INGREDIENTS:

Chelidonium Majus 3X, Glycyrrhiza Glabra 3X, Nux Moschata 3X, Rheum 3X, Syzygium Jambolanum 3X, Taraxacum Officinale 3X, Zingiber Officinale 3X, Hydrastis Canadensis 5X, Glandula Suprarenalis Suis 6X, Hepar Suis 6X, Hypophysis Suis 6X, Pancreas 6X, Thyroidinum 8X, Phaseolus 12X, Phosphoricum Acidum 12X, Phosphorus 12X.

PURPOSE:

For temporary relief of nervous anxiety, afternoon headache, feeling faint relieved by eating, craving of sweets, nervousness if meals missed.

WARNINGS:

If pregnant or breast-feeding, ask a health care professional before use.

Keep out of reach of children. In case of overdose, get medical help or contact a Poison Control Center right away.

Do not use if tamper evident seal is broken or missing.

Store in a cool, dry place.

KEEP OUT OF REACH OF CHILDREN:

In case of overdose, get medical help or contact a Poison Control Center right away.

DIRECTIONS:

10 drops orally, 3 times a day. Consult a physician for use in children under 12 years of age.

INDICATIONS:

For temporary relief of nervous anxiety, afternoon headache, feeling faint relieved by eating, craving of sweets, nervousness if meals missed.

INACTIVE INGREDIENTS:

Demineralized Water, 25% Ethanol

QUESTIONS:

Distributed by:
BioActive Nutritional, Inc.
1803 N. Wickham Rd.
Melbourne, FL 32935
bioactivenutritional.com

PACKAGE LABEL DISPLAY:

BIOActiveNutritional

PANCREAPLEX

HOMEOPATHIC

1 FL OZ (30 ml)